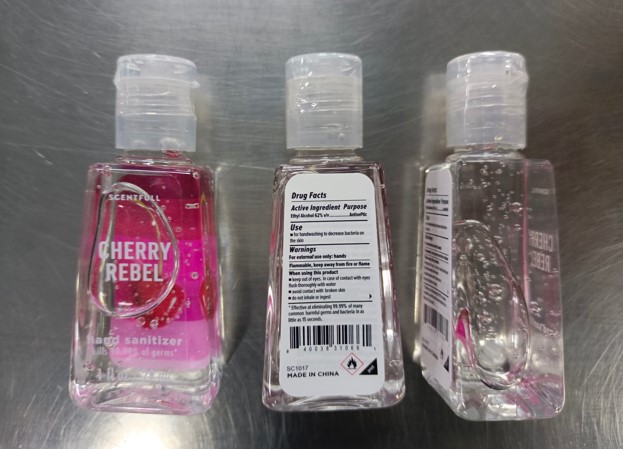 DRUG LABEL: HAND SANITIZER
NDC: 76891-136 | Form: GEL
Manufacturer: SCENT THEORY PRODUCTS LLC
Category: otc | Type: HUMAN OTC DRUG LABEL
Date: 20240607

ACTIVE INGREDIENTS: ALCOHOL 62 mL/100 mL
INACTIVE INGREDIENTS: WATER; CARBOMER 940; AMINOMETHYLPROPANOL; GLYCERIN; ALOE VERA LEAF; DENATONIUM BENZOATE

SCENTFULL - HAND SANITIZER 62% ALCOHOL - REBEL CHERRY (76891-136)

ACTIVE INGREDIENT

ALCOHOL 62% V/V

PURPOSE

ANTISEPTIC

USES

FOR HANDWASHING TO DECREASE BACTERIA ON HANDS.

WARNINGS

FOR EXTERNAL USE ONLY: HANDS

FLAMMABLE, KEEP AWAY FROM FIRE OR FLAME.

WHEN USING THIS PRODUCT

- KEEP OUT OF EYES. IN CASE OF CONTACT WITH EYES, FLUSH THOROUGHLY WITH WATER.
- AVOID CONTACT WITH BROKEN SKIN.
- DO NOT INHALE OR INGEST.

Keep out of reach of children. If swallowed, get medical help or contact a Poison Control Center right away.

DIRECTIONS

- SHAKE WELL BEFORE USING.
- DISPENSE A GOLF BALL SIZED AMOUNT ONTO HANDS
- RUB HANDS TOGETHER UNTIL DRY
- ENJOY THE LUCIOUS SCENT

INACTIVE INGREDIENTS

WATER (AQUA), FRAGRANCE (PARFUM), CARBOMER, AMINOMETHYL PROPANOL, GLYCERIN, DENATONIUM BENZOATE, ALOE BARBADENSIS LEAF JUICE.